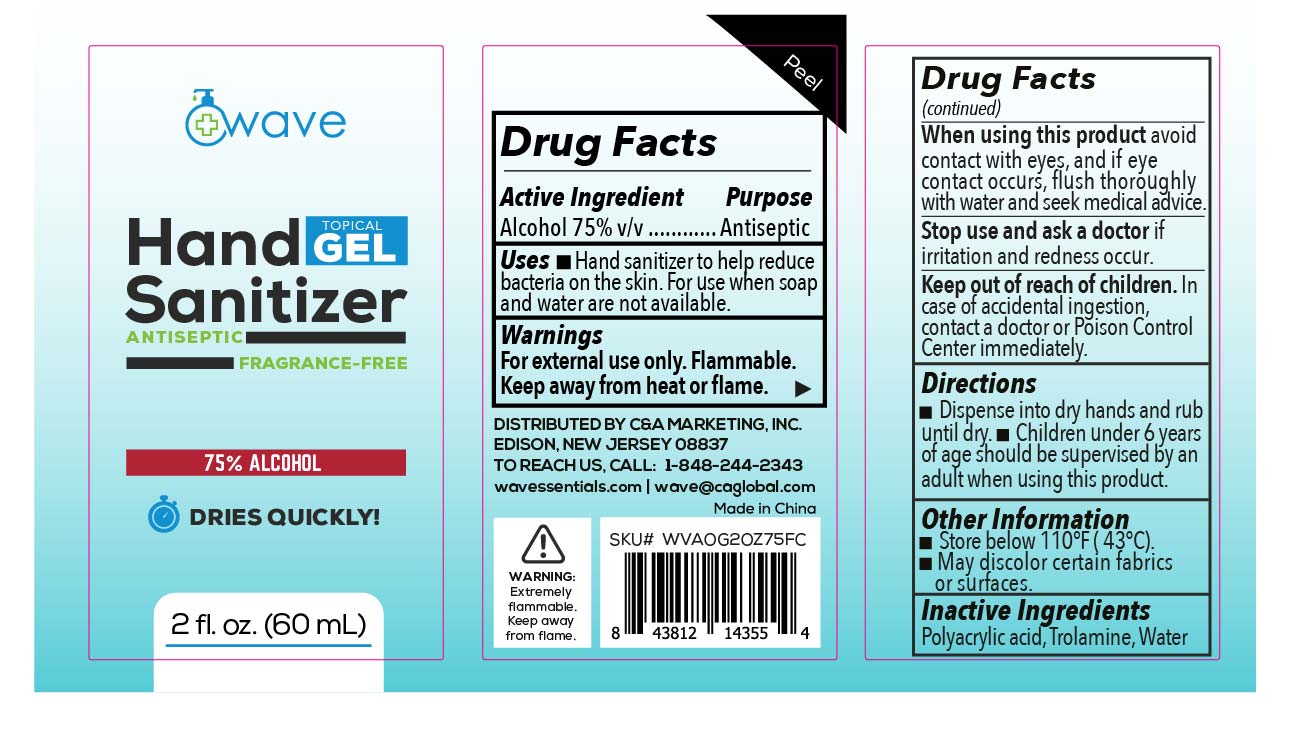 DRUG LABEL: Wave Hand Sanitizer
NDC: 78754-003 | Form: GEL
Manufacturer: C & A MARKETING, INC.
Category: otc | Type: HUMAN OTC DRUG LABEL
Date: 20210202

ACTIVE INGREDIENTS: ALCOHOL 75 mL/100 mL
INACTIVE INGREDIENTS: TROLAMINE; POLYACRYLIC ACID (250000 MW); WATER

New CA Global AO Wave Sanitizer Gel 75

Active Ingredient

Alcohol 75%v/v

Purpose

Antiseptic

Uses

■ Hand Sanirtizer to help reduce bacteria on the skin. For use when soap and water are not available.

Warnings

For external use only. Flammable. Keep away from heat or flame

When using this product

avoid contact with eyes, and if eye contact occurs, flush thoroughly with water and seek medical advice

Stop use and ask a doctor

if irritation and redness occur.

Keep out of reach of children

In case of accidentail ingestion, contact a doctor or Poison Control Center immediately.

Directions

■ Dispense into dry hands and rub until dry. ■ Children under 6 years of age should be supervised by an adult when using this product.

Other information

■ Store below 110ºF (43ºC) ■ May discolor certain fabrics or surfaces.

Inactive ingredients

Polyacrylic acid, Trolamine, Water